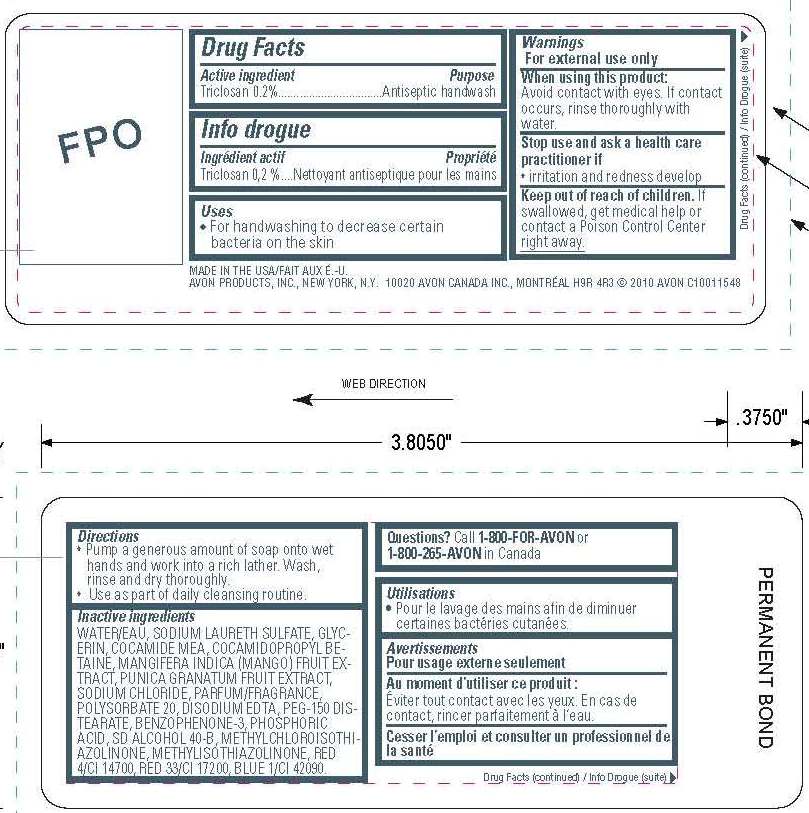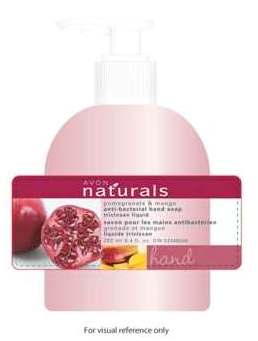 DRUG LABEL: Naturals Pomegranate and Mango
NDC: 10096-0209 | Form: LIQUID
Manufacturer: New Avon LLC
Category: otc | Type: HUMAN OTC DRUG LABEL
Date: 20160212

ACTIVE INGREDIENTS: TRICLOSAN 2 mg/1 mL

Active ingredient
Triclosan 0.20%.......................

Purpose

..................Antiseptic handwash

Uses

- for handwashing to decrease certain bacteria on the skin

Warnings
For external use only

When using this product:
Avoid contact with eyes. If contact occurs, rinse thoroughly with water.

Stop use and ask a healthcare practitioner if

- irritation and redness develop

Keep out of reach of children. If swallowed, get medical help or contact a poison control center right away.

Directions

- Pump a generous amount of soap onto wet hands and work into a rich lather. Wash, rinse and dry thoroughly.
- Use as part of daily cleansing routine.

Inactive Ingredients

WATER/EAU
SODIUM LAURETH SULFATE
GLYCERIN
COCAMIDE MEA
COCAMIDOPROPYL BETAINE
MANGIFERA INDICA (MANGO) FRUIT EXTRACT
PUNICA GRANATUM FRUIT EXTRACT
SODIUM CHLORIDE
PARFUM/FRAGRANCE
POLYSORBATE 20
DISODIUM EDTA
PEG-150 DISTEARATE
BENZOPHENONE-3
PHOSPHORIC ACID
SD ALCOHOL 40-B
METHYLCHLOROISOTHIAZOLINONE
METHYLISOTHIAZOLINONE
RED 4/CI 14700
RED 33/CI 17200
BLUE 1/CI 42090

QUESTIONS

Questions? Call 1-800-FOR-AVON or 1-800-265-AVON in Canada